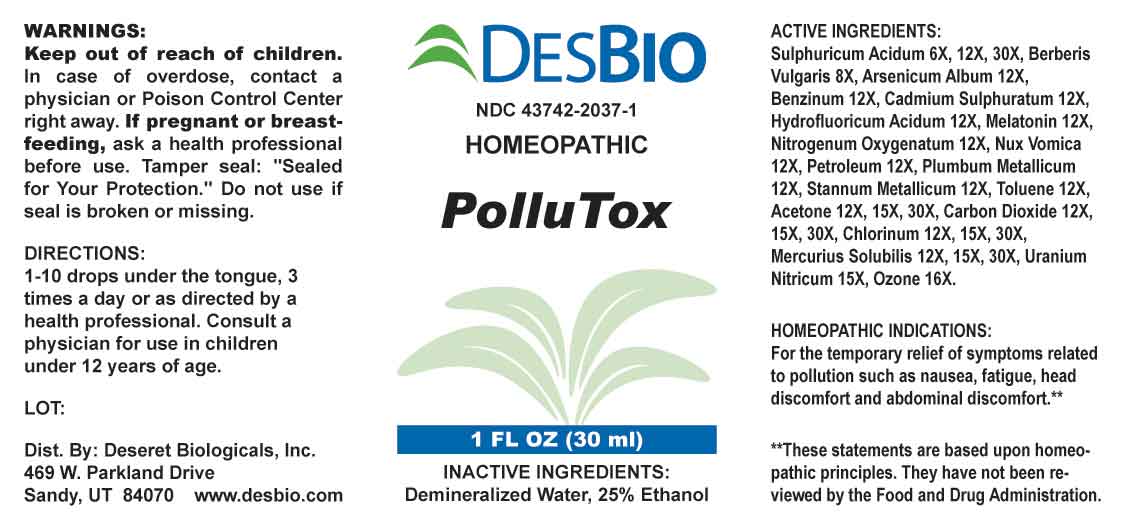 DRUG LABEL: Pollutox
NDC: 43742-2037 | Form: LIQUID
Manufacturer: Deseret Biologicals, Inc.
Category: homeopathic | Type: HUMAN OTC DRUG LABEL
Date: 20231026

ACTIVE INGREDIENTS: SULFURIC ACID 6 [hp_X]/1 mL; BERBERIS VULGARIS ROOT BARK 8 [hp_X]/1 mL; ARSENIC TRIOXIDE 12 [hp_X]/1 mL; BENZENE 12 [hp_X]/1 mL; CADMIUM SULFIDE 12 [hp_X]/1 mL; HYDROFLUORIC ACID 12 [hp_X]/1 mL; MELATONIN 12 [hp_X]/1 mL; NITROUS OXIDE 12 [hp_X]/1 mL; STRYCHNOS NUX-VOMICA SEED 12 [hp_X]/1 mL; KEROSENE 12 [hp_X]/1 mL; LEAD 12 [hp_X]/1 mL; TIN 12 [hp_X]/1 mL; TOLUENE 12 [hp_X]/1 mL; ACETONE 12 [hp_X]/1 mL; CARBON DIOXIDE 12 [hp_X]/1 mL; CHLORINE 12 [hp_X]/1 mL; MERCURIUS SOLUBILIS 12 [hp_X]/1 mL; URANYL NITRATE HEXAHYDRATE 15 [hp_C]/1 mL; OZONE 16 [hp_X]/1 mL
INACTIVE INGREDIENTS: WATER; ALCOHOL

DRUG FACTS:

ACTIVE INGREDIENTS:

Sulphuricum Acidum 6X, 12X, 30X, Berberis Vulgaris 8X, Arsenicum Album 12X, Benzinum 12X, Cadmium Sulphuratum 12X, Hydrofluoricum Acidum 12X, Melatonin 12X, Nitrogenum Oxygenatum 12X, Nux Vomica 12X, Petroleum 12X, Plumbum Metallicum 12X, Stannum Metallicum 12X, Toluene 12X, Acetone 12X, 15X, 30X, Carbon Dioxide 12X, 15X, 30X, Chlorinum 12X, 15, 30, Mercurius Solubilis 12X, 15, 30, Uranium Nitricum 15C, Ozone 16X.

PURPOSE:

For the temporary relief of symptoms related to pollution such as nausea, fatigue, head discomfort and abdominal discomfort.**

**These statements are based upon homeopathic principles. They have not been reviewed by the Food and Drug Administration.

WARNINGS:

Keep out of reach of children. In case of overdose, contact a physician or Poison Control Center right away.

If pregnant or breast-feeding, ask a health professional before use.

Tamper Seal: "Sealed for Your Protection."

Do not use if seal is broken or missing.

KEEP OUT OF REACH OF CHILDREN:

In case of overdose, contact a physician or Poison Control Center right away.

DIRECTIONS:

1-10 drops under the tongue, 3 times a day or as directed by a health professional. Consult a physician for use in children under 12 years of age.

INDICATIONS:

For the temporary relief of symptoms related to pollution such as nausea, fatigue, head discomfort and abdominal discomfort.**

**These statements are based upon homeopathic principles. They have not been reviewed by the Food and Drug Administration.

INACTIVE INGREDIENTS:

Demineralized Water, 25% Ethanol

QUESTIONS:

Dist. By: Deseret Biologicals, Inc.

469 W. Parkland Drive

Sandy, UT 84070 www.desbio.com

PACKAGE LABEL DISPLAY:

DESBIO
NDC 43742-2037-1
HOMEOPATHIC

PolluTox

1 FL OZ (30 ml)